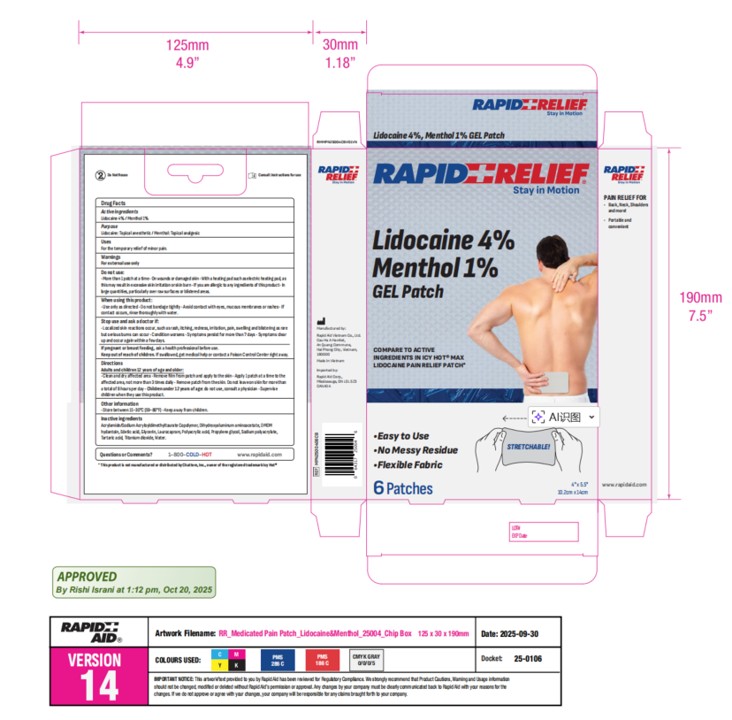 DRUG LABEL: Rapid Relief
NDC: 83569-016 | Form: PATCH
Manufacturer: RAPID AID VIET NAM COMPANY LIMITED
Category: otc | Type: HUMAN OTC DRUG LABEL
Date: 20251113

ACTIVE INGREDIENTS: LIDOCAINE 4 g/100 g; MENTHOL 1 g/100 g
INACTIVE INGREDIENTS: GLYCERIN; EDETATE DISODIUM ANHYDROUS; TARTARIC ACID; TITANIUM DIOXIDE; SODIUM POLYACRYLATE (8000 MW); DMDM HYDANTOIN; DIHYDROXYALUMINUM AMINOACETATE; PROPYLENE GLYCOL; LAUROCAPRAM; POLYACRYLIC ACID (800000 MW); WATER; ACRYLAMIDE/SODIUM ACRYLOYLDIMETHYLTAURATE COPOLYMER (120000 MPA.S AT 1%)

Active Ingredient(s)

Lidocaine 4 % +Menthol 1% w/w.

Purpose

Lidocaine: Topical anesthetic / Menthol: Topical analgesic

Use

For the temporary relief of minor pain.

Warnings

For external use only.

Do not use

More than 1 patch at a time
On wounds or damaged skin
With a heating pad such as electric heating pad,as this may result in excessive skin irritation or skin burn
If you are allergic to any ingredients of this product

In large quantities, particularly over raw surfaces or blistered areas

When using this product:

Use only as directed

Do not bandage tightly

Avoid contact with eyes, mucous membranes or rashes

If contact occurs, rinse thoroughly with water

Stop use and ask a doctor if:

Localized skin reactions occur, such as rash, itching, redness, irritation, pain, swelling and blistering

Condition worsens

Symptoms persist for more than 7 days

Symptoms clear up and occur again within a few days

If pregnant or breastfeeding, ask a health professional before use.

Keep out of reach of children. If swallowed, get medical help or contact a Poison Control Center right away.

Directions

Adults and children 12 years of age and older:

Clean and dry affected area

Remove film from patch and apply to the skin

Apply 1 patch at a time to the affected area, not more than 3 times daily.

Remove patch from the skin.

Do not leave on skin for more than a total of 8 hours per day

Children under 12 years of age:

Do not use, consult a physician.

Supervise children when they use this product

STORAGE AND HANDLING

Store between 15-30℃(59-86℉) keep away from children

Inactive ingredients

Acryloyldime/ Sodium Acryloyldimethyltaurate copolymer, Dihydroxyaluminum aminoacetetel, DMDM hydantoin, Edetic acid,, Glycerin, Laurocapram，Polyacrylic acid, Propylene glycol, Sodium polyacrylate, Tartaric acid, Titanium dioxide, Water